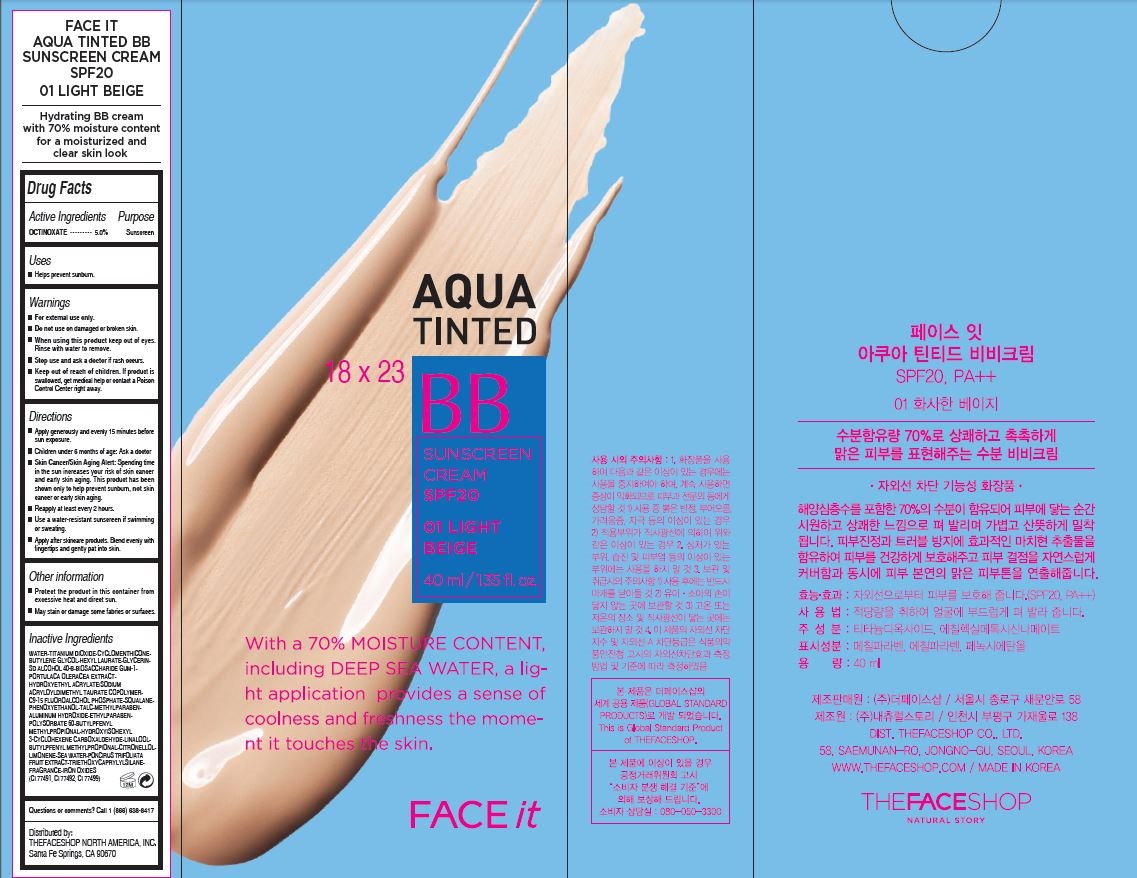 DRUG LABEL: FACE IT AQUA TINTED
NDC: 51523-420 | Form: CREAM
Manufacturer: THEFACESHOP CO., LTD.
Category: otc | Type: HUMAN OTC DRUG LABEL
Date: 20141120

ACTIVE INGREDIENTS: OCTINOXATE 2 g/40 mL
INACTIVE INGREDIENTS: WATER

Face It Aqua Tinted 32800420

Active Ingredients

OCTINOXATE...5.0%

Purpose

Sunscreen

Uses

Helps prevent sunburn.

Warnings

For external use only.

Do not use on damaged or broken skin.

When using this product keep out of eyes.

Rinse with water to remove.

Stop use and ask a doctor if rash occurs.

Keep out of reach of children.

If product is swallowed, get medical help or contact a Poison

Control Center right away.

Directions

Apply generously and evenly 15 minutes before

sun exposure.

Children under 6 months of age: Ask a doctor

Skin Cancer/Skin Aging Alert: Spending time

in the sun increases your risk of skin cancer

and early skin aging. This product has been

shown only to help prevent sunburn, not skin

cancer or early skin aging.

Reapply at least every 2 hours.

Use a water-resistant sunscreen if swimming

or sweating.

Apply after skincare products.

Blend evenly with fingertips and gently pat into skin.

Other information

Protect the product in this container from

excessive heat and direct sun.

May stain or damage some fabrics or surfaces.

Inactive Ingredients

WATER•TITANIUM DIOXIDE•CYCLOMENTHICONE•

BUTYLENE GLYCOL•HEXYL LAURATE•GLYCERIN•

SD ALCOHOL 40-B•BIOSACCHARIDE GUM-1•

PORTULACA OLERACEA EXTRACT•

HYDROXYETHYL ACRYLATE/SODIUM

ACRYLOYLDIMETHYL TAURATE COPOLYMER•

C9-15 FLUOROALCOHOL PHOSPHATE•SQUALANE•

PHENOXYETHANOL•TALC•METHYLPARABEN•

ALUMINUM HYDROXIDE•ETHYLPARABEN•

POLYSORBATE 60•BUTYLPFENYL

METHYLPROPIONAL•HYDROXYISOHEXYL

3-CYCLOHEXENE CARBOXALDEHYDE•LINALOOL•

BUTYLPFENYL METHYLPROPIONAL•CITRONELLOL•

LIMONENE•SEA WATER•PONCIRUS TRIFOLIATA

FRUIT EXTRACT•TRIETHOXYCAPRYLYLSILANE•

FRAGRANCE•IRON OXIDES

(CI 77491, CI 77492, CI 77499)

Questions or comments? Call 1 (866) 638-8417

Distributed by:

THEFACESHOP NORTH AMERICA, INC.

Santa Fe Springs, CA 90670

PACKAGE LABEL

AQUA TINTED

BB

SUNSCREEN CREAM SPF20

01 LIGHT BEIGE

With a 70% MOISTURE CONTENT, including DEEP SEA WATER,

a light application provides a sense of coolness and freshness the moment it touches the skin.

FACE it